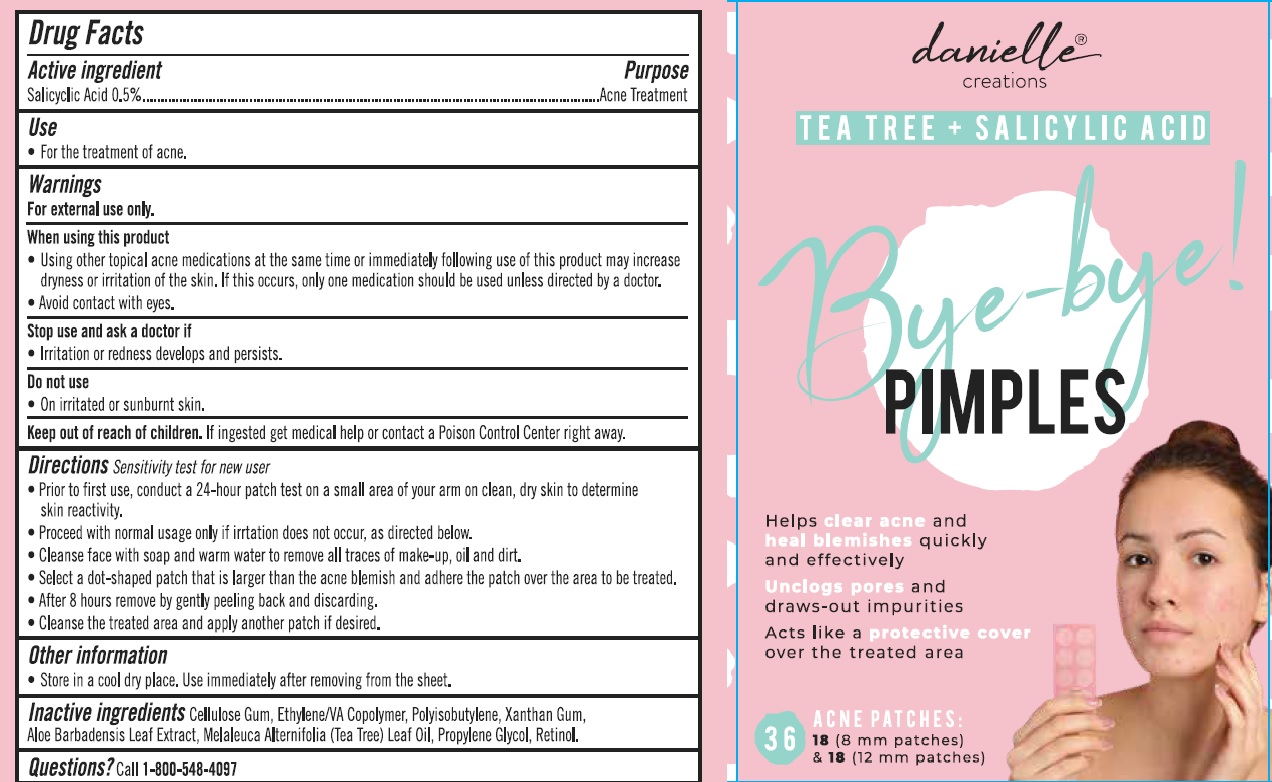 DRUG LABEL: Bye-Bye Pimples
NDC: 78936-025 | Form: PATCH
Manufacturer: Hangzhou Caring Cleaning Commodity Co., LTD
Category: otc | Type: HUMAN OTC DRUG LABEL
Date: 20210531

ACTIVE INGREDIENTS: SALICYLIC ACID 0.5 1/1 1
INACTIVE INGREDIENTS: CARBOXYMETHYLCELLULOSE SODIUM; ETHYLENE-VINYL ACETATE COPOLYMER (9% VINYLACETATE); POLYISOBUTYLENE (1000 MW); XANTHAN GUM; ALOE VERA LEAF; TEA TREE OIL; PROPYLENE GLYCOL; RETINOL

Drug Facts

Active ingredient

Salicylic Acid 0.5%

Purpose

Acne treatment

Use

For the treatment of acne

Warnings

For external use only.

When using this product

- Using other topical acne medications at the same time or immediately following use of this product may increase dryness or irritation of the skin. If this occurs, only one medication should be used unless directed by a doctor.
- Avoid contact with eyes.

Stop use and ask a doctor

- if irritation or redness develops and persists.

Do not use

- On irritated or sunburnt skin.

Keep out of reach of children.

If ingested get medical help or contact a Poison Control Center right away.

Directions

Sensitivity test for new user

- Prior to first use, conduct a 24-hour patch test on a samll area of your arm on clean, dry skin to determine skin reactivity.
- Proceed with normal usage only if irritation does not occur, as directed below:
- Cleanse face with soap and warm water to remove all traces of make-up, oil and dirt.
- Select a dot-shaped patch that is larger than the acne blemish and adhere the patch over the area to be treated.
- After 8 hours remove by gently peeling back and discarding.
- Cleanse the treated area and apply another patch if desired.

Other information

- Store in a cool dry place. Use immediately after removing from the sheet.

Inactive ingredients

Cellulose Gum, Ethylene/VA Copolymer, Polyisobutylene, Xanthan Gum, Aloe Barbadensis Leaf Extract, Melaleuca Alternifolia (Tea Tree) Leaf Oil, Propylene Glycol, Retinol.

Questions?

Call 1-800-548-4097